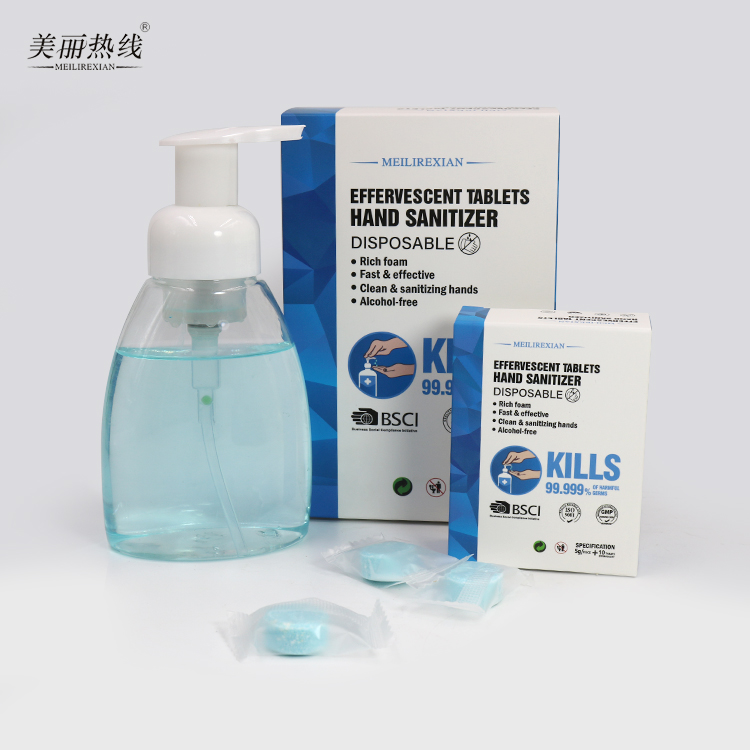 DRUG LABEL: Effervescent Hand Sanitizer
NDC: 75111-901 | Form: TABLET
Manufacturer: Enping Jiaxin Daily Necessities Co., Ltd.
Category: otc | Type: HUMAN OTC DRUG LABEL
Date: 20210202

ACTIVE INGREDIENTS: BENZALKONIUM CHLORIDE 8 1/100 1
INACTIVE INGREDIENTS: ALOE VERA LEAF; CITRIC ACID MONOHYDRATE; SODIUM SULFATE; SODIUM BICARBONATE; CETYLPYRIDINIUM CHLORIDE; POLYETHYLENE GLYCOL 400; GLYCERIN

Effervescent Hand Sanitizer

Active Ingredient(s)

Benzalkonium Chloride 8%. Purpose: Antiseptic

Purpose

Antiseptic, Clean&sanitizing hands

Use

Disposable Effervescent Tablets Hand Sanitizer to help reduce bacteria that potentially can cause disease. For use when soap and water are not available.

Warnings

For external use only. Flammable. Keep away from heat or flame

Do not use

- in children less than 2 months of age
- on open skin wounds

When using this product keep out of eyes, ears, and mouth. In case of contact with eyes, rinse eyes thoroughly with water.
Stop use and ask a doctor if irritation or rash occurs. These may be signs of a serious condition.
Keep out of reach of children. If swallowed, get medical help or contact a Poison Control Center right away.

Stop use and ask a doctor if irritation or rash occurs. These may be signs of a serious condition.

Keep out of reach of children. If swallowed, get medical help or contact a Poison Control Center right away.

Directions

- After dissolution, place enough product on hands to cover all surfaces. Rub hands together until dry.
- Supervise children under 6 years of age when using this product to avoid swallowing.

Other information

- Store between 15-30C (59-86F)
- Avoid freezing and excessive heat above 40C (104F)

Inactive ingredients

Sodium Bicarbonate, Citric Acid, Sodium Sulfate, Cetylpyridinium Chloride, PEG-8, Glycerin, Aloe Barbadensis Leaf Extract